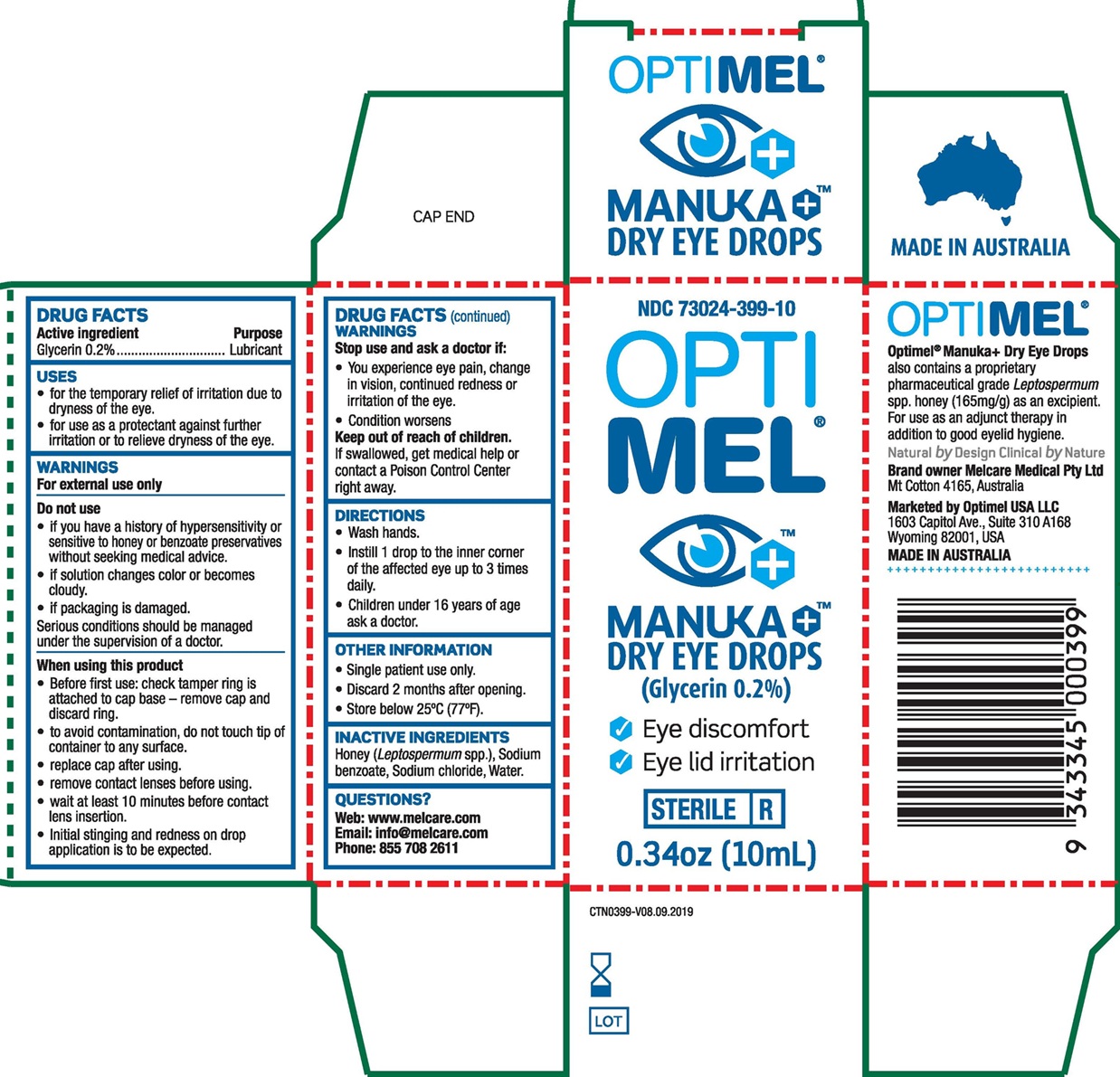 DRUG LABEL: Optimel Manuka Dry Eye Drops
NDC: 73024-399 | Form: SOLUTION/ DROPS
Manufacturer: Melcare Biomedical Pty Ltd
Category: otc | Type: HUMAN OTC DRUG LABEL
Date: 20251209

ACTIVE INGREDIENTS: GLYCERIN 2 mg/1 mL
INACTIVE INGREDIENTS: HONEY; WATER; SODIUM CHLORIDE; SODIUM BENZOATE

Optimel Manuka+ Dry Eye Drops

Drug Facts

Active ingredients

Glycerin 0.2%

Purpose

Lubricant

Uses

- for the temporary relief of burning and irritation due to dryness of the eye.
- for use as a protectant against further irritation or to relieve dryness of the eye.

Warnings

For external use only

Do not use

- if you have a history of hypersensitivity or sensitive to honey or benzoate preservatives without seeking medical advice.
- if solution changes color or becomes cloudy.
- if packaging is damaged.
- serious conditions should be managed under the supervision of a doctor.

When using this product

- Before first use: check tamper ring is attached to cap base – remove cap and discard ring.
- to avoid contamination, do not touch tip of container to any surface.
- replace cap after using.
- remove contact lenses before using.
- wait at least 10 minutes before contact lens insertion.
- Initial stinging and redness on drop application is to be expected.

Stop use and ask a doctor if

- You experience eye pain change in vision, continued redness or irritation of the eye.
- Condition worsens

Keep out of reach of children.

If swallowed, get medical help or contact a Poison Control Center right away.

Directions

- Wash hands.
- Instill 1 drop to the inner corner of the affected of the affected eye up to 3 times daily.
- Children under 16 years of age ask a doctor.

Other information

- Single patient use only.
- Discard 2 months after opening.
- Store below 25°C (77°F).

Inactive ingredients

Honey (Leptospermum spp.), Sodium benzoate, Sodium chloride, Water.

Questions?

Web: www.melcare.com
Email: info@melcare.com
Phone: 8557082611